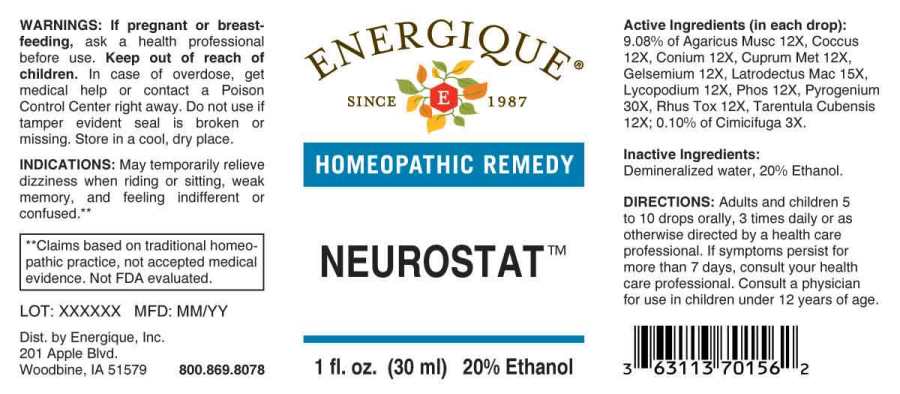 DRUG LABEL: Neurostat
NDC: 44911-0217 | Form: LIQUID
Manufacturer: Energique, Inc.
Category: homeopathic | Type: HUMAN OTC DRUG LABEL
Date: 20230712

ACTIVE INGREDIENTS: BLACK COHOSH 3 [hp_X]/1 mL; AMANITA MUSCARIA FRUITING BODY 12 [hp_X]/1 mL; PROTORTONIA CACTI 12 [hp_X]/1 mL; CONIUM MACULATUM FLOWERING TOP 12 [hp_X]/1 mL; COPPER 12 [hp_X]/1 mL; GELSEMIUM SEMPERVIRENS ROOT 12 [hp_X]/1 mL; LYCOPODIUM CLAVATUM SPORE 12 [hp_X]/1 mL; PHOSPHORUS 12 [hp_X]/1 mL; TOXICODENDRON PUBESCENS LEAF 12 [hp_X]/1 mL; CITHARACANTHUS SPINICRUS 12 [hp_X]/1 mL; LATRODECTUS MACTANS 15 [hp_X]/1 mL; RANCID BEEF 30 [hp_X]/1 mL
INACTIVE INGREDIENTS: WATER; ALCOHOL

Drug Facts:

ACTIVE INGREDIENTS:

(in each drop): 9.08% of Agaricus Muscarius 12X, Coccus Cacti 12X, Conium Maculatum 12X, Cuprum Metallicum 12X, Gelsemium Sempervirens 12X, Latrodectus Mactans 15X, Lycopodium Clavatum 12X, Phosphorus 12X, Pyrogenium 30X, Rhus Tox 12X, Tarentula Cubensis 12X; 0.10% of Cimicifuga Racemosa 3X.

INDICATIONS:

May temporarily relieve dizziness when riding or sitting, weak memory, and feeling indifferent or confused.**

**Claims based on traditional homeopathic practice, not accepted medical evidence. Not FDA evaluated.

WARNINGS:

If pregnant or breast-feeding, ask a health professional before use.

Keep out of reach of children. In case of overdose, get medical help or contact a Poison Control Center right away.

Do not use if tamper evident seal is broken or missing. Store in a cool, dry place.

Keep out of reach of children. In case of overdose, get medical help or contact a Poison Control Center right away.

DIRECTIONS:

Adults and children 5 to 10 drops orally, 3 times daily or as otherwise directed by a health care professional. If symptoms persist for more than 7 days, consult your health care professional. Consult a physician for use in children under 12 years of age.

INDICATIONS:

May temporarily relieve dizziness when riding or sitting, weak memory, and feeling indifferent or confused.**

**Claims based on traditional homeopathic practice, not accepted medical evidence. Not FDA evaluated.

INACTIVE INGREDIENTS:

Demineralized water, 20% Ethanol.

QUESTIONS:

Dist. by Energique, Inc.

201 Apple Blvd

Woodbine, IA 51579 800.869.8078

PACKAGE LABEL DISPLAY:

ENERGIQUE
SINCE 1987
HOMEOPATHIC REMEDY
NEUROSTAT
1 fl. oz. (30 ml)